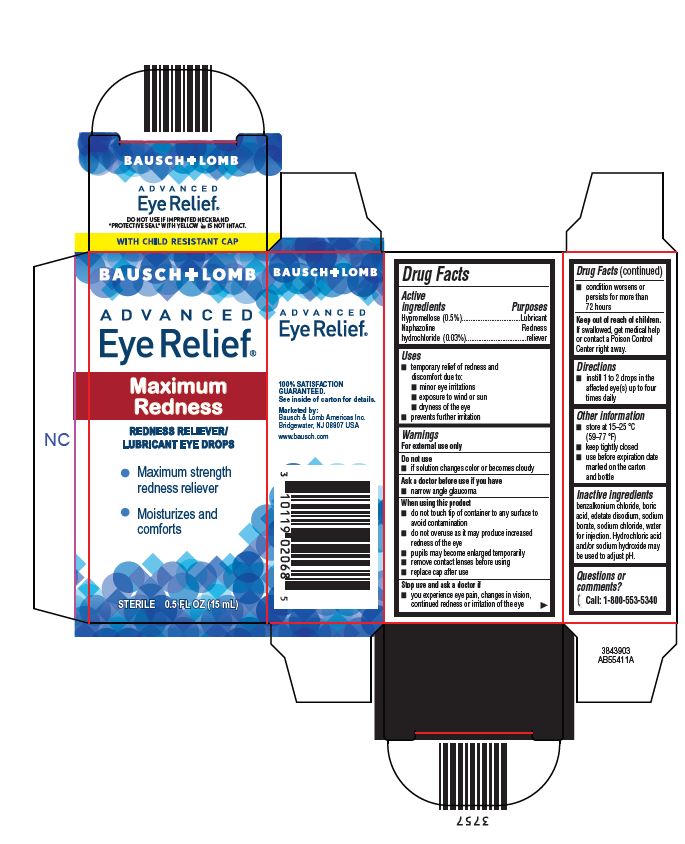 DRUG LABEL: Advanced Eye Relief/ Redness Maximum Relief
NDC: 24208-450 | Form: SOLUTION/ DROPS
Manufacturer: Bausch & Lomb Incorporated
Category: otc | Type: HUMAN OTC DRUG LABEL
Date: 20240925

ACTIVE INGREDIENTS: HYPROMELLOSE, UNSPECIFIED 5 mg/1 mL; NAPHAZOLINE HYDROCHLORIDE 0.3 mg/1 mL
INACTIVE INGREDIENTS: BENZALKONIUM CHLORIDE; BORIC ACID; EDETATE DISODIUM; WATER; SODIUM BORATE; SODIUM CHLORIDE; HYDROCHLORIC ACID; SODIUM HYDROXIDE

Drug Facts

Active ingredients

Hypromellose (0.5%)
Naphazoline hydrochloride (0.03%)

Purpose

Lubricant
Redness reliever

Uses

- temporary relief of redness and discomfort due to:
  - minor eye irritations
  - exposure to wind or sun
  - dryness of the eye
- prevents further irritation

Warnings

For external use only

Do not use

- if solution changes color or becomes cloudy

Ask a doctor before use if you have

- narrow angle glaucoma

When using this product

- do not touch tip of container to any surface to avoid contamination
- do not overuse as it may produce increased redness of the eye
- pupils may become enlarged temporarily
- remove contact lenses before using
- replace cap after use

Stop use and ask a doctor if

- you experience eye pain, changes in vision, continued redness or irritation of the eye
- condition worsens or persists for more than 72 hours

Keep out of reach of children.

If swallowed, get medical help or contact a Poison Control Center right away.

Directions

- instill 1 to 2 drops in the affected eye(s) up to four times daily

Other information

- store at 15–25 °C (59–77 °F)
- keep tightly closed
- use before expiration date marked on the carton and bottle

Inactive ingredients

benzalkonium chloride, boric acid, edetate disodium, sodium borate, sodium chloride, water for injection. Hydrochloric acid and/or sodium hydroxide may be used to adjust pH.

Questions or comments?

[phone icon] Call: 1-800-553-5340

Package/Label Principal Display Panel

BAUSCH + LOMB
ADVANCED
Eye Relief®
Maximum
Redness
REDNESS RELIEVER/
LUBRICANT EYE DROPS

- Maximum strength
  redness reliever
- Moisturizes and
  comforts

STERILE 0.5 FL OZ (15 mL)

3843903
AB55411A